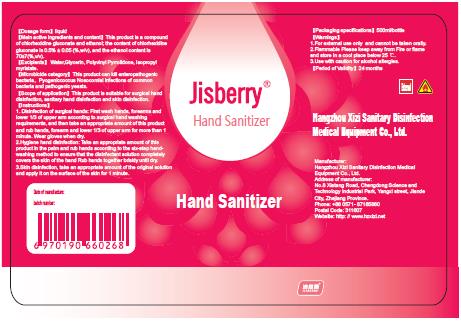 DRUG LABEL: Jisberry Hand Sanitizer
NDC: 52738-004 | Form: LIQUID
Manufacturer: Hangzhou Xizi Sanitary Disinfection Medical Equipment Co., Ltd.
Category: otc | Type: HUMAN OTC DRUG LABEL
Date: 20200414

ACTIVE INGREDIENTS: CHLORHEXIDINE GLUCONATE 2.5 mg/500 mL; ALCOHOL 350 mL/500 mL
INACTIVE INGREDIENTS: POVIDONE; GLYCERIN; WATER

DOSAGE AND ADMINISTRATION

Flammable Please keep away from Fire or flame and store in a cool place below 25 C.

INACTIVE INGREDIENT

Water

Glycerin

Polyvinyl Pyrrolidone

Isopropyl myristate

ACTIVE INGREDIENT

Ethyl alcohol

Chlorhexidine digluconate

keep out of children

PURPOSE

Disinfection
Sterilization

WARNINGS

1.For external use only and cannot be taken orally
2.Flammable Please keep away from Fire or flame and store in a cool place below 25 C.
3.Use with caution for alcohol allergies.